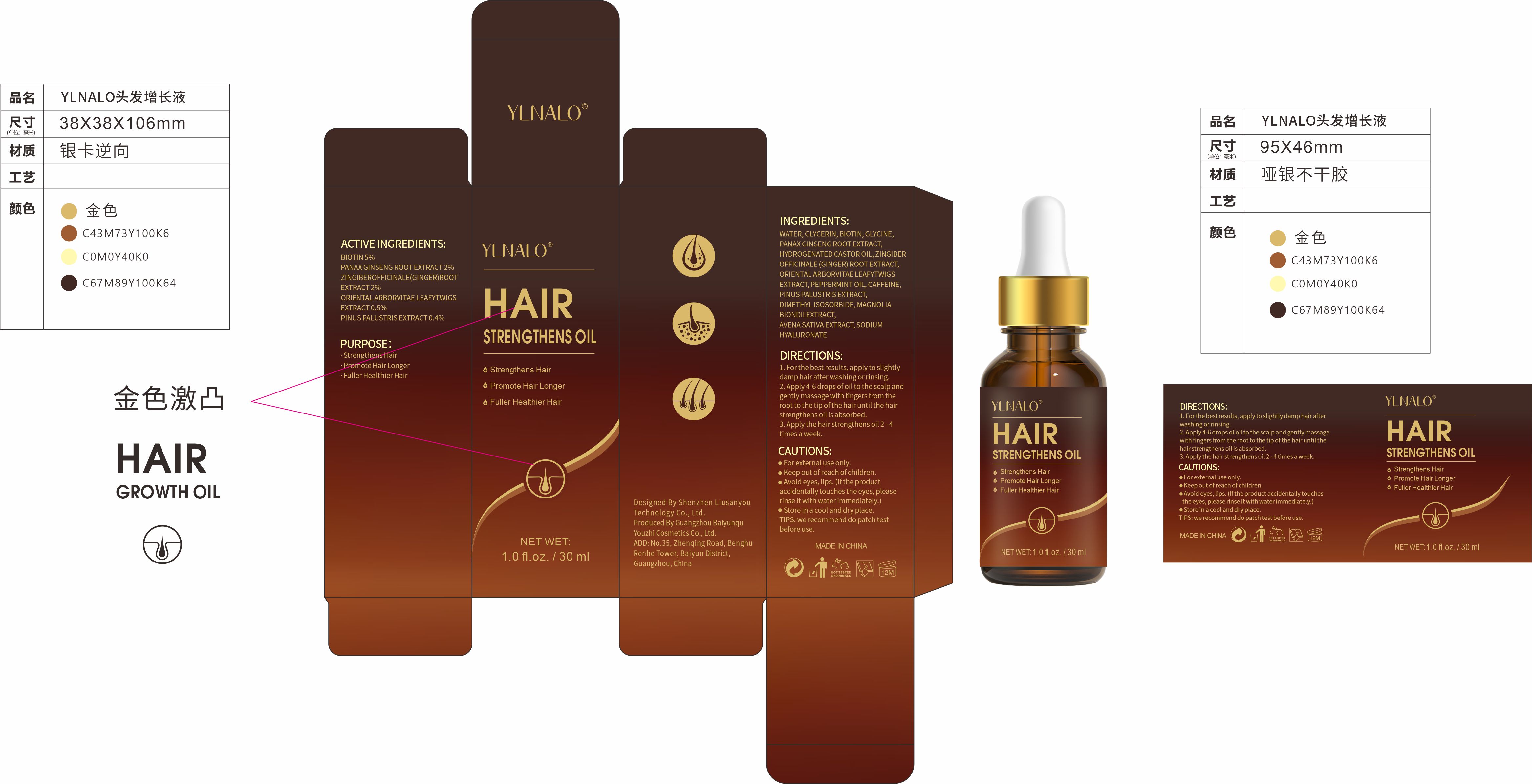 DRUG LABEL: Hair Strengthens Oil
NDC: 83604-101 | Form: OIL
Manufacturer: Shenzhen Xiyue Electronic Commerce Co., Ltd.
Category: otc | Type: HUMAN OTC DRUG LABEL
Date: 20230821

ACTIVE INGREDIENTS: GLYCERIN 0.05 mg/100 mL; AMENTOFLAVONE 0.5 mg/100 mL; BIOTIN 5 mg/100 mL; ASIAN GINSENG 2 mg/100 mL; PINUS PALUSTRIS LEAF 0.4 mg/100 mL; GINGER 2 mg/100 mL
INACTIVE INGREDIENTS: DIMETHYL ISOSORBIDE; HYDROGENATED CASTOR OIL; PEPPERMINT OIL; MEDIORESINOL DIMETHYL ETHER; OAT; WATER; GLYCINE; HYALURONATE SODIUM; CAFFEINE

HAIR STRENGTHENS OIL

HAIR STRENGTHENS OIL

ACTIVE INGREDIENT

BIOTIN 5%
PANAX GINSENG ROOT EXTRACT 2%
ZINGIBER OFFICINALE (GINGER) ROOT EXTRACT 2%
ORIENTAL ARBORVITAE LEAFYTWIGS EXTRACT 0.5%
PINUS PALUSTRIS EXTRACT 0.4%

PURPOSE

Strengthens Hair

Promote Hair Longer

Fuller Healthier Hair

INDICATIONS AND USAGE

Strengthens Hair

Promote Hair Longer
Fuller Healthier Hair

WARNINGS

For externaluse only.
Keep out of reach of children.

For externaluse only.
Keep out of reach of children.
Avoid eyes, lips. (lfthe productaccidentally touches the eyes, pleaserinse it with water immediately.)

TIPS: we recommend do patch testbefore use.

Avoid eyes, lips. (lfthe productaccidentally touches the eyes, pleaserinse it with water immediately.)

WHEN USING

For externaluse only.
Keep out of reach of children.
Avoid eyes, lips. (lfthe productaccidentally touches the eyes, pleaserinse it with water immediately.)

STOP USE

If discomfort occurs, immediately stop using and seek medical advice

Keep out of reach of children.

DOSAGE AND ADMINISTRATION

1. Forthe best results, apply to slightlydamp hair after washing or rinsing
2. Apply 4-6 drops of oil to the scalp andgently massage with fingers from theroot to the tip ofthe hair untilthe hairstrengthens oilis absorbed
3. Apply the hair strengthens oil 2 - 4times a week

STORAGE AND HANDLING

Store in a cooland dry place

INACTIVE INGREDIENT

WATER
GLYCERIN
GLYCINE
HYDROGENATED CASTOR OIL
PEPPERMINT OIL
CAFFEINE
DIMETHYL ISOSORBIDE
MAGNOLIA BIONDII EXTRACT
AVENA SATIVA EXTRACT
SODIUM HYALURONATE